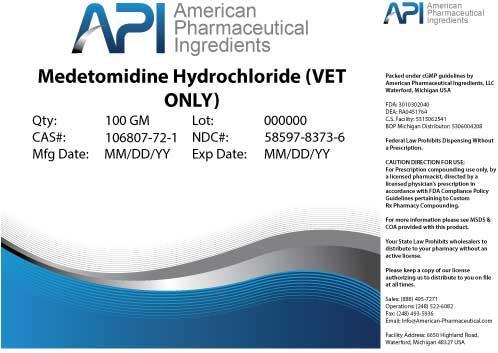 DRUG LABEL: Medetomidine Hydrochloride
NDC: 58597-8373 | Form: POWDER
Manufacturer: AMERICAN PHARMACEUTICAL INGREDIENTS LLC
Category: other | Type: BULK INGREDIENT
Date: 20140428

ACTIVE INGREDIENTS: Medetomidine Hydrochloride 1 g/1 g

Medetomidine Hydrochloride